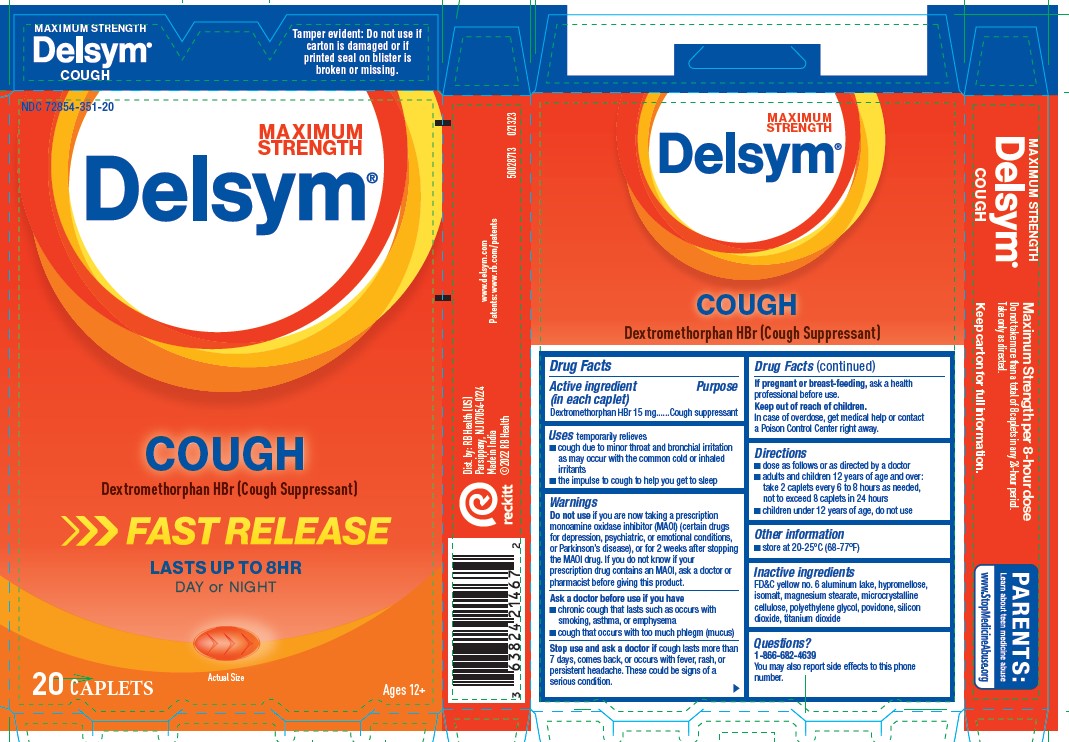 DRUG LABEL: Delsym Cough
NDC: 72854-351 | Form: TABLET
Manufacturer: RB Health (US) LLC
Category: otc | Type: HUMAN OTC DRUG LABEL
Date: 20241223

ACTIVE INGREDIENTS: DEXTROMETHORPHAN HYDROBROMIDE 15 mg/1 1
INACTIVE INGREDIENTS: FD&C YELLOW NO. 6; HYPROMELLOSE, UNSPECIFIED; ISOMALT; MAGNESIUM STEARATE; MICROCRYSTALLINE CELLULOSE; POLYETHYLENE GLYCOL, UNSPECIFIED; POVIDONE, UNSPECIFIED; SILICON DIOXIDE; TITANIUM DIOXIDE

Delsym® Cough

Drug Facts

Active ingredient (in each caplet)

Dextromethorphan HBr 15 mg

Purpose

Cough suppressant

Use

temporarily relieves

- cough due to minor throat and bronchial irritation as may occur with the common cold or inhaled irritants
- the impulse to cough to help you get to sleep

Warnings

Do not use if you are now taking a prescription monoamine oxidase inhibitor (MAOI) (certain drugs for depression, psychiatric, or emotional conditions, or Parkinson's disease), or for 2 weeks after stopping the MAOI drug. If you do not know if your prescription drug contains an MAOI, ask a doctor or pharmacist before taking this product.

Ask a doctor before use if you have

- chronic cough that lasts such as occurs with smoking, asthma, or emphysema
- cough that occurs with too much phlegm (mucus)

Stop use and ask a doctor if cough lasts more than 7 days, comes back, or occurs with fever, rash, or persistent headache. These could be signs of a serious condition.

PREGNANCY OR BREAST FEEDING

If pregnant or breast-feeding, ask a health professional before use.

Keep out of reach of children.

In case of overdose, get medical help or contact a Poison Control Center right away.

Directions

- dose as follows or as directed by a doctor
- adults and children 12 years of age and over:
  take 2 caplets every 6 to 8 hours as needed, not to exceed 8 caplets in 24 hours
- children under 12 years of age:
  do not use

Other information

- store at 20-25°C (68-77°F)

Inactive ingredients

FD&C yellow no. 6 aluminum lake, hypromellose, isomalt, magnesium stearate, microcrystalline cellulose, polyethylene glycol, povidone, silicon dioxide, titanium dioxide

Questions?

1-866-682-4639

You may also report side effects to this phone number.

Dist. by: RB Health (US)
Parsippany, NJ 07054-0224
Made in India

PRINCIPAL DISPLAY PANEL - 20 Caplet Blister Pack Carton

MAXIMUM STRENGTH

NEW!

NDC 72854-351-20

Delsym®

COUGH
Dextromethorphan HBr (Cough Suppressant)

LASTS
UP
TO
8HR

DAY
OR
NIGHT

FAST
RELEASE

Actual Size

20 Caplets
For Ages 12+